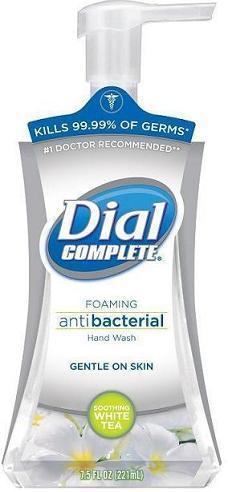 DRUG LABEL: Dial Complete Antibacterial Foaming Hand Wash
NDC: 54340-503 | Form: SOLUTION
Manufacturer: The Dial Corporation
Category: otc | Type: HUMAN OTC DRUG LABEL
Date: 20130325

ACTIVE INGREDIENTS: TRICLOSAN 4.6 mg/1 mL
INACTIVE INGREDIENTS: WATER; SODIUM XYLENESULFONATE; DIPROPYLENE GLYCOL; GLYCERIN; SODIUM PYRROLIDONE CARBOXYLATE; AMMONIUM LAURYL SULFATE; COCAMIDOPROPYL BETAINE; POLYQUATERNIUM-10 (400 MPA.S AT 2%); SODIUM PHOSPHATE, DIBASIC, ANHYDROUS; CETYL ALCOHOL; GREEN TEA LEAF; CITRIC ACID MONOHYDRATE; METHYLPARABEN; PROPYLPARABEN; PROPYLENE GLYCOL; EXT. D&C VIOLET NO. 2

Drug Facts

Active Ingredient - TRICLOSAN 0.46%

PURPOSE

Antibacterial

INDICATIONS AND USAGE

For hand washing to decrease bacteria on the skin

WARNINGS

For external use only.

When using this product avoid contact with eyes. In case of eye contact, flush with water.

Stop use and ask a doctor if irritation and redness develops.

Keep out of reach of children. If swallowed, get medical help or contact a Poison Control Center right away.

DOSAGE AND ADMINISTRATION

Directions: Pump into dry hands. Lather vigorously for 15 seconds. Rinse and dry thoroughly.

INACTIVE INGREDIENT

Inactive Ingredients: Water, Sodium Xylenesulfonate, Dipropylene Glycol, Glycerin, Sodium PCA, Camellia Sinensis Leaf Extract (White Tea Extract), Ammonium Lauryl Sulfate, Cocamidopropyl Betaine, Polyquaternium-10, Fragrance, Disodium Phosphate, Cetyl Alcohol, Propylene Glycol, Citric Acid, Methylparaben, Propylparaben, Ext. Violet 2.

Questions? 1-800-258-DIAL

221 ml Label image